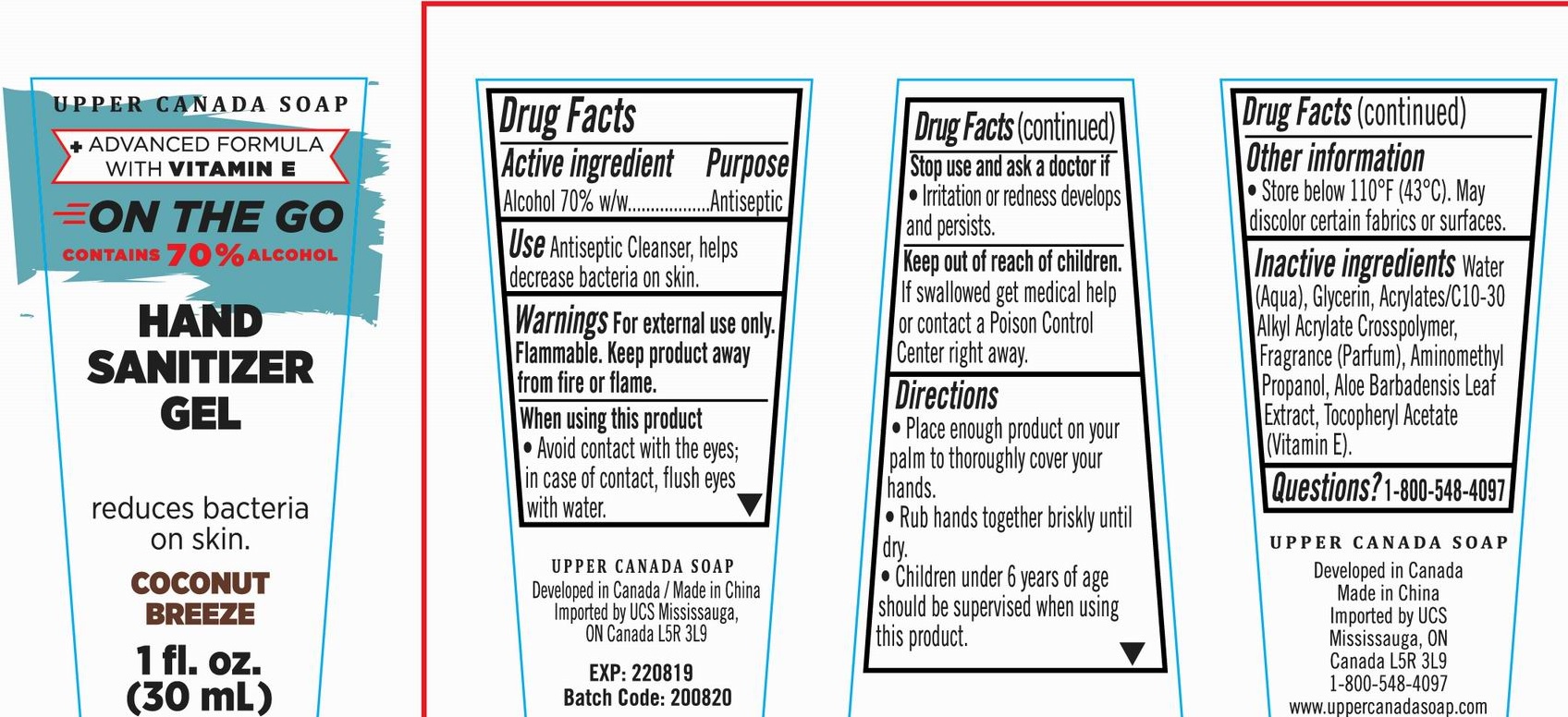 DRUG LABEL: On The Go HAND SANITIZER Coconut Breeze
NDC: 56136-224 | Form: GEL
Manufacturer: Ganzhou Olivee Cosmetic Co., Ltd.
Category: otc | Type: HUMAN OTC DRUG LABEL
Date: 20201009

ACTIVE INGREDIENTS: ALCOHOL 70 mL/100 mL
INACTIVE INGREDIENTS: WATER; GLYCERIN; ALPHA-TOCOPHEROL; CARBOMER COPOLYMER TYPE A; AMINOMETHYLPROPANOL; ALOE VERA LEAF

HAND SANITIZER

Active ingredient

Alcohol 70% w/w

Purpose

Antiseptic

Use

Antiseptic Cleanser, Help decrease bacteria on skin.

Warnings

For external use only.

Flammable. Keep product away from fire or flame.

When using this product

avoid contact with eyes; in case of contact, flush eyes with water.

Stop use and ask a doctor if

irritation or redness develops and persists.

Keep out of reach of children.

If swallowed, get medical help or contact a Poison Control Center right away.

Directions

- Place enough product on your palm to thoroughly cover your hads.
- Rub hands together briskly until dry.
- Children under 6 years of age should be supervised when using this product.

Inactive ingredients

Water (Aqua), Glycerin, ACRYLATES/C10-30 ALKYL ACRYLATE CROSSCOPOLYMER, Fragrance (Parfum), AMINOMETHYL PROPANOL, Aloe Barbadensis Leaf Extract, Tocopheryl Actate (Vitamin E).

Other information:

Store below 110℉ （43℃）. May discolor certain fabrics or surfaces.